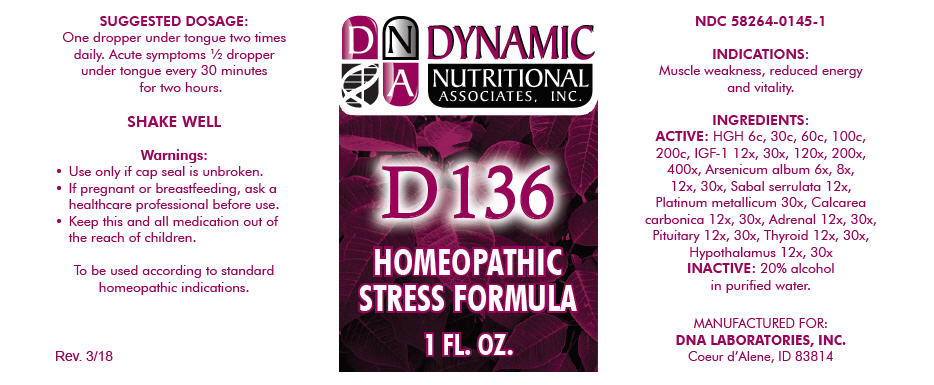 DRUG LABEL: D-136
NDC: 58264-0145 | Form: SOLUTION
Manufacturer: DNA Labs, Inc.
Category: homeopathic | Type: HUMAN OTC DRUG LABEL
Date: 20250113

ACTIVE INGREDIENTS: SOMATROPIN 12 [hp_X]/1 mL; LONG-(ARG3)INSULIN-LIKE GROWTH FACTOR-I 12 [hp_X]/1 mL; ARSENIC TRIOXIDE 6 [hp_X]/1 mL; SAW PALMETTO 12 [hp_X]/1 mL; PLATINUM 30 [hp_X]/1 mL; OYSTER SHELL CALCIUM CARBONATE, CRUDE 12 [hp_X]/1 mL; BOS TAURUS ADRENAL CORTEX 12 [hp_X]/1 mL; BOS TAURUS PITUITARY GLAND, POSTERIOR 12 [hp_X]/1 mL; THYROID, UNSPECIFIED 12 [hp_X]/1 mL; BOS TAURUS HYPOTHALAMUS 12 [hp_X]/1 mL
INACTIVE INGREDIENTS: ALCOHOL; WATER

D-136

NDC 58264-0145-1

INDICATIONS

PURPOSE

Muscle weakness, reduced energy and vitality.

INGREDIENTS

ACTIVE

HGH 6c, 30c, 60c, 100c, 200c, IGF-1 12x, 30x, 120x, 200x, 400x, Arsenicum album 6x, 8x, 12x, 30x, Sabal serrulata 12x, Platinum metallicum 30x, Calcarea carbonica 12x, 30x, Adrenal 12x, 30x, Pituitary 12x, 30x, Thyroid 12x, 30x, Hypothalamus 12x, 30x

INACTIVE

20% alcohol in purified water.

SUGGESTED DOSAGE

One dropper under tongue two times daily. Acute symptoms ½ dropper under tongue every 30 minutes for two hours.

STORAGE AND HANDLING

SHAKE WELL

Warnings

- Use only if cap seal is unbroken.

PREGNANCY OR BREAST FEEDING

- If pregnant or breastfeeding, ask a healthcare professional before use.

KEEP OUT OF REACH OF CHILDREN

- Keep this and all medication out of the reach of children.

To be used according to standard homeopathic indications.

PRINCIPAL DISPLAY PANEL - 1 FL. OZ. Bottle Label

DYNAMIC
NUTRITIONAL
ASSOCIATES, INC.

D 136

HOMEOPATHIC
STRESS FORMULA

1 FL. OZ.